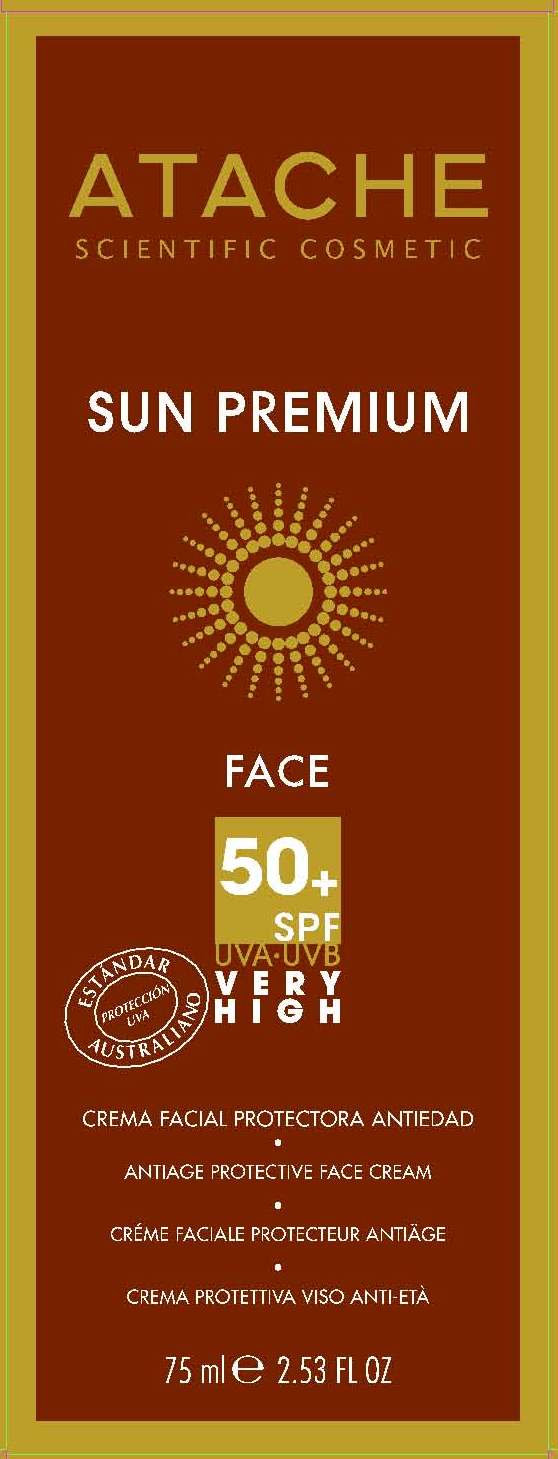 DRUG LABEL: SUN PREMIUM FACE 50 SPF
NDC: 75870-006 | Form: CREAM
Manufacturer: LABORATORIOS DE COSMETICA SCIENTIFICA ATACHE SA
Category: otc | Type: HUMAN OTC DRUG LABEL
Date: 20110616

ACTIVE INGREDIENTS: OXYBENZONE 3.75 mL/75 mL; OCTINOXATE 3.75 mL/75 mL; AVOBENZONE 1.5 mL/75 mL; TITANIUM DIOXIDE 1.185 mL/75 mL
INACTIVE INGREDIENTS: WATER; ALOE VERA LEAF; UREA; CETOSTEARYL ALCOHOL; GLYCERIN; C12-20 ALKYL BENZOATE; ISOHEXADECANE; TRIETHYLHEXANOIN; CETYL PALMITATE; DIMETHICONE; TRIMETHOXYCAPRYLYLSILANE; STEARETH-2; SHEA BUTTER; PHENOXYETHANOL; METHYLPARABEN; ETHYLPARABEN; PROPYLPARABEN; BUTYLPARABEN; CYCLOMETHICONE; CETETH-25; PEG-9 STEARATE; DOCOSANOL; SODIUM PYRROLIDONE CARBOXYLATE; GLYCERETH-26; STEARETH-21; SQUALANE; PARAFFIN; DIAZOLIDINYL UREA; ECHINACEA ANGUSTIFOLIA; CENTELLA ASIATICA; FUCUS VESICULOSUS; FENUGREEK SEED; PROPYLENE GLYCOL; CASTOR OIL; ALCOHOL; POLYOXYL 60 HYDROGENATED CASTOR OIL; CALCIUM PANTOTHENATE; INOSITOL; BIOTIN; RETINOL; .ALPHA.-TOCOPHEROL ACETATE, D-; GLYCERYL LINOLEATE; GLYCERYL LINOLENATE; GLYCERYL ARACHIDONATE; ALUMINUM STEARATE; ALUMINUM OXIDE; XANTHAN GUM; ALLANTOIN; COCONUT OIL; GARDENIA TAITENSIS FLOWER; LIMONENE, (+)-; LINALOOL, DL-; EDETATE SODIUM; HYDROXYSTEARIC ACID; .ALPHA.-TOCOPHEROL ACETATE, D-; DIPALMITOYL HYDROXYPROLINE

SUN PREMIUM FACE 50+ SPF

PACKAGE LABEL

ATACHE

SCIENTIFIC COSMETIC

SUN PREMIUM

FACE
50+ SPF
UVA-UVB
VERY
HIGH
COLOR
ANTIAGE PROTECTIVE FACE CREAM
WITH COLOR
75 ml e 2.53 FL OZ

DESCRIPTION

ANTIAGE PROTECTIVE FACE CREAM

WITH COLOR

Innovative combination of a selection of extracts that offer a perfect balance between sun protection and beauty. A soft, pleasant texture on your skin, that lets you enjoy an even tan while it protects your face from the signs of ageing and gives a firmer appearance.

INSTRUCTIONS FOR USE: Apply evenly to the face and neck half an hour before sunbathing. Apply again each 1-2 hours or after bathing.

WARNINGS

WARNINGS: For external use only. Keep out of reach of children. Avoid contact with eyes. Discontinue use if signs of irritation of rash appear.

ACTIVE INGREDIENTS:

OXYBENZONE 5% - sunscreen

OCTINOXATE 5% - sunscreen

AVOBENZONE 2% - sunscreen

TITANIUM DIOXIDE 1.5% - sunscreen

INACTIVE INGREDIENT

OTHER INGREDIENTS: AQUA (WATER), ALOE VERA GEL, UREA, CETEARYL ALCOHOL, GLLYCERIN, C12-20 ALKYL BENZOATE, ISOHEXADECANE, TRIETHYLEXANOIN, CETYL PALMITATE, DIMETHICONE, TRIMETHOXYCAPRYLYLSILANE, STEARETH-2, BUTYROSPERMUM PARK II (SHEA BUTTER), PHENOXYETHANOL, METHYLPARABEN, ETHYLPARABEN, PROPYLPARABEN, BUTYLPARABEN, CYCLOMETHICONE, DIMETHICONOL, CETETH-25, PEG-0 STEARATE, BEHENYL ALCOHOL, SODIUM PCA, GLYCERETH-26, STEARETH-21, SQUALANE, PARAFFIN, DIAZOLIDINYL UREA, ECHINACEA ANTUSTIFOLIA EXTRACT, CENTELLA ASIATICA EXTRACT, FUCUS VESICULOSUS EXTRACT, TRIGONELLA FOENUM-GRAECUM SEED EXTRACT, PROPYLENE GLYCOL, PEG-20 CASTOR OIL, ALCOHOL DENAT, PEG-60 HYDROGENATED CASTOR OIL, CALCIUM PANTOTHENATE, INOSITOL, BIOTIN, RETINOL, TOCOPHERYL ACETATE, GLYCERYL LINOLEATE, GLYCERYL LINOLENATE, GLYCERYL ARACHIDONATE, ALUMINIUM STEARATE, ALUMINA, XANTHAN GUM, ALLANTOIN, COCOS NUCIFERA (COCONUM OIL), GARDENIA TAHITENSIS (TIARE FLOWER), PARFUM (FRAGRANCE), LIMONENE, LINALOOL, TETRASODIUM EDTA, POLYHYDROXYESTEARIC ACID, TOCOPHERYL ACETATE, DIPALMITOYL HYDROXYPROLINE.

PACKAGE LABEL

Enter section text here